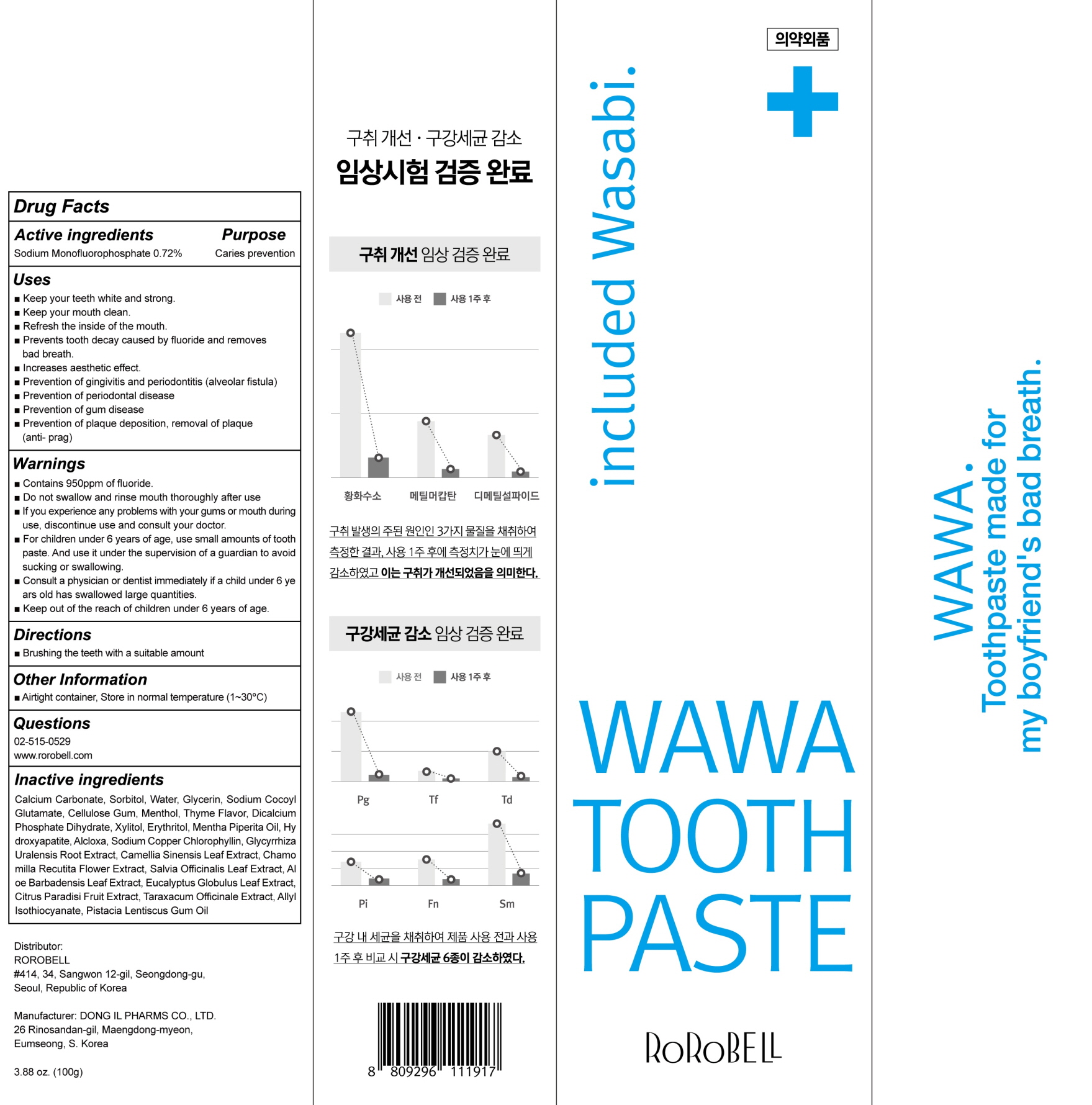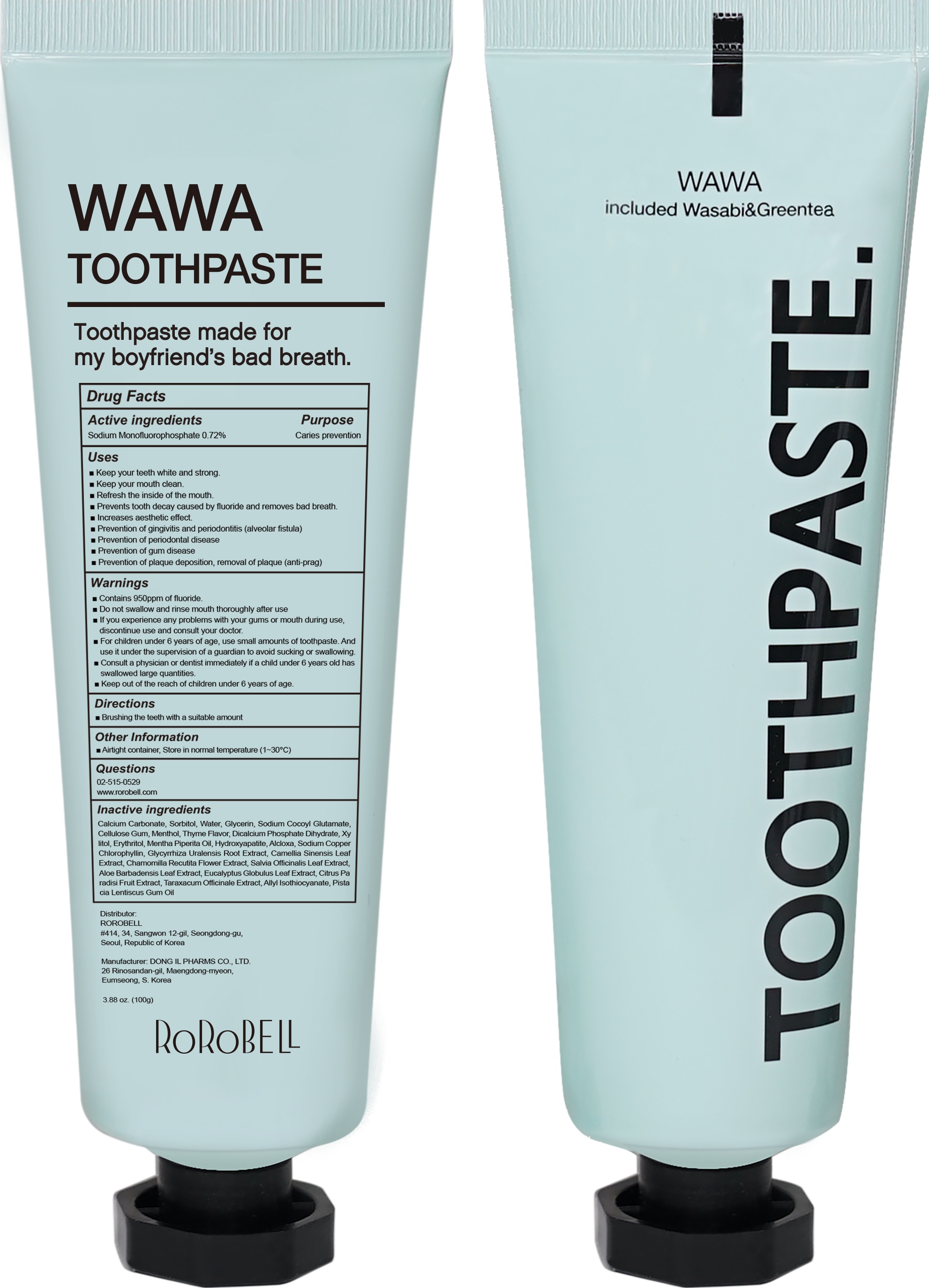 DRUG LABEL: Rorobell WaWa Tooth
NDC: 81275-010 | Form: PASTE, DENTIFRICE
Manufacturer: ROROBELL
Category: otc | Type: HUMAN OTC DRUG LABEL
Date: 20251020

ACTIVE INGREDIENTS: SODIUM MONOFLUOROPHOSPHATE 0.72 g/100 g
INACTIVE INGREDIENTS: CALCIUM CARBONATE; DIBASIC CALCIUM PHOSPHATE DIHYDRATE; ALUMINUM CHLOROHYDRATE

ACTIVE INGREDIENT

Sodium Monofluorophosphate 0.72%

INACTIVE INGREDIENTS

Calcium Carbonate, Sorbitol, Water, Glycerin, Sodium Cocoyl Glutamate, Cellulose Gum, Menthol, Thyme Flavor, Dicalcium Phosphate Dihydrate, Xylitol, Erythritol, Mentha Piperita Oil, Hydroxyapatite, Alcloxa, Sodium Copper Chlorophyllin, Glycyrrhiza Uralensis Root Extract, Camellia Sinensis Leaf Extract, Chamomilla Recutita Flower Extract, Salvia Officinalis Leaf Extract, Aloe Barbadensis Leaf Extract, Eucalyptus Globulus Leaf Extract, Citrus Paradisi Fruit Extract, Taraxacum Officinale Extract, Allyl Isothiocyanate, Pistacia Lentiscus Gum Oil

PURPOSE

Caries prevention

WARNINGS

■ Contains 950ppm of fluoride.
■ Do not swallow and rinse mouth thoroughly after use
■ If you experience any problems with your gums or mouth during use,
discontinue use and consult your doctor.
■ For children under 6 years of age, use small amounts of toothpaste. And use it
under the supervision of a guardian to avoid sucking or swallowing.
■ Consult a physician or dentist immediately if a child under 6 years old has
swallowed large quantities.
■ Keep out of the reach of children under 6 years of age.

KEEP OUT OF REACH OF CHILDREN

Keep out of the reach of children under 6 years of age.

Uses

■ Keep your teeth white and strong.
■ Keep your mouth clean.
■ Refresh the inside of the mouth.
■ Prevents tooth decay caused by fluoride and removes bad breath.
■ Increases aesthetic effect.
■ Prevention of gingivitis and periodontitis (alveolar fistula)
■ Prevention of periodontal disease
■ Prevention of gum disease
■ Prevention of plaque deposition, removal of plaque (anti-prag)

Directions

■ Brushing the teeth with a suitable amount

Other Information

Airtight container, Store in normal temperature (1~30℃)

QUESTIONS

02-515-0529
www.rorobell.com